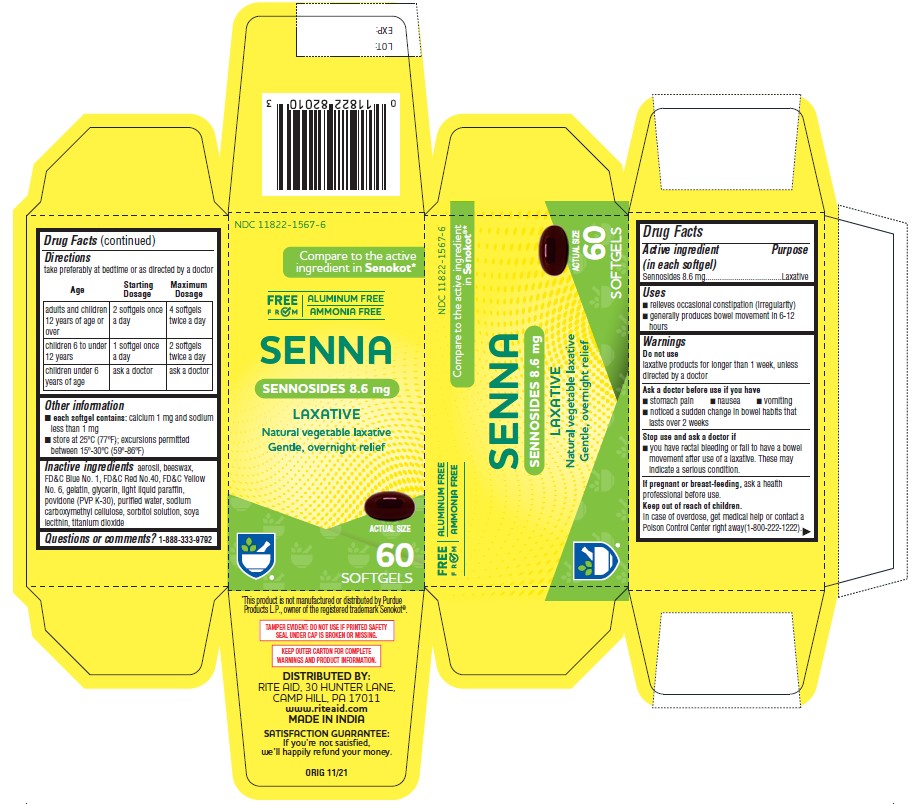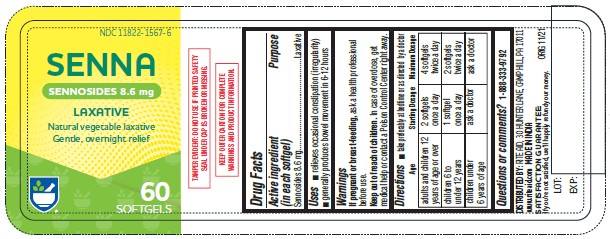 DRUG LABEL: SENNA
NDC: 11822-1571 | Form: CAPSULE, LIQUID FILLED
Manufacturer: RITE AID CORPORATION
Category: otc | Type: HUMAN OTC DRUG LABEL
Date: 20241230

ACTIVE INGREDIENTS: SENNOSIDES 8.6 mg/1 1
INACTIVE INGREDIENTS: SILICON DIOXIDE; SYNTHETIC BEESWAX; FD&C BLUE NO. 1; FD&C RED NO. 40; FD&C YELLOW NO. 6; GELATIN; GLYCERIN; PARAFFIN; POVIDONE K30; CARBOXYMETHYLCELLULOSE SODIUM; SORBITOL SOLUTION; LECITHIN, SOYBEAN; TITANIUM DIOXIDE; WATER

SENNA

Active Ingredient (in each Softgel)

Sennosides 8.6 mg

Purpose

Laxative

Uses

• relieves occasional constipation (irregularity) • generally produces bowel movement in 6–12 hours

Warnings

Do not use laxative products for longer than 1 week, unless directed by a doctor

Ask a doctor before use if you have • stomach pain • nausea • vomiting • noticed a sudden change in bowel habits that lasts over 2 weeks

Stop use and ask a doctor if • you have rectal bleeding or fail to have a bowel movement after use of a laxative. These may indicate a serious condition

PREGNANCY OR BREAST FEEDING

If pregnant or breast-feeding, ask a health professional before use.

Keep out of reach of children. In case of overdose, get medical help or contact a Poison Control Center right away (1-800-222-1222).

Directions

take preferably at bedtime or as directed by a doctor

Age | Starting Dosage | Maximum Dosage
adults & children 12 years of age & over | 2 softgels once a day | 4 softgels twice a day
children 6 to under 12 years of age | 1 softgels once a day | 2 softgels twice a day
children under 6 years of age | ask a doctor | ask a doctor

Other information

• each softgel contains: calcium 1 mg and sodium less than 1 mg
• store at 25°C (77°F); excursions permitted between 15°–30°C (59°–86°F)

Inactive ingredients

aerosil, beeswax, FD&C Blue No. 1, FD&C Red No.40, FD&C Yellow
No. 6, gelatin, glycerin, light liquid paraffin, povidone (PVP K-30), purified water, sodium carboxymethyl cellulose, sorbitol solution, soya lecithin, titanium dioxide

Questions or comments?

1-888-333-9792

Distributed by:
RITE AID
30 Hunter Lane, Camp Hill, PA 17011
www.riteaid.com
Made in India